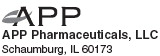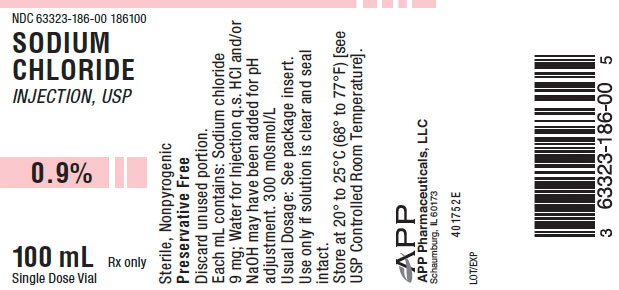 DRUG LABEL: Sodium Chloride
NDC: 63323-186 | Form: INJECTION
Manufacturer: Fresenius Kabi USA, LLC
Category: prescription | Type: HUMAN PRESCRIPTION DRUG LABEL
Date: 20251128

ACTIVE INGREDIENTS: SODIUM CHLORIDE 9 mg/1 mL
INACTIVE INGREDIENTS: HYDROCHLORIC ACID; SODIUM HYDROXIDE

Sodium Chloride Injection USP

0.9%

DESCRIPTION

Sodium Chloride Injection, USP, 0.9% is a sterile, nonpyrogenic solution. Each mL contains: Sodium chloride 9 mg; Water for Injection, q.s. Sodium Chloride Injection, USP, 0.9% contains no preservative or added buffer. The osmolarity is 300 mOsmol per liter.

Hydrochloric acid and/or sodium hydroxide may have been added for pH adjustment (4.5-7.0).

Sodium chloride occurs as colorless cubic crystals or white crystalline powder and has a saline taste. Sodium chloride is freely soluble in water. It is soluble in glycerin and slightly soluble in alcohol.

The empirical formula for sodium chloride is NaCl, and the molecular weight is 58.44.

CLINICAL PHARMACOLOGY

Sodium chloride comprises over 90% of the inorganic constituents of the blood serum. Both its ions are physiologically important. Sodium, more than any other ion, determines the osmotic pressure of interstitial fluids and the degree of hydration of tissues. When the intake of the chloride ion is less than is excreted, there is a relative increase in the blood bicarbonate level, producing the condition known as alkalosis. Other symptoms of sodium chloride deficiency are nausea and vomiting and increased irritability of muscles, evidenced by cramps and possibly convulsions. It is well known that excessive sweating will cause ‘‘heatcramps,’’ i.e., muscle cramps in the abdomen and extremities, which can be completely relieved only by ingestion of a weak salt solution.

Approximately 25% of the total body sodium is found in the bone. The regulation of salt and water metabolism is governed by different mechanisms; however, changes in the intake distribution and output of salt are, in health, associated with collateral shifts of water so that electrolyte concentrations are maintained within a narrow range. In the presence of disease affecting the cardiovascular, hepatic or renal system or in certain endocrinologic disorders, changes in the rate of excretion of salt and water will disturb the homeostatic equilibrium. Frequently, abnormalities in the metabolism of water or salt may occur as a result of vomiting, diarrhea, gastrointestinal suction and fever. Excessive sweating will produce loss of water or salt, but since the electrolyte concentration is hypotonic, loss of water will predominate.

The normal salt intake ranges from 5 to 15 grams daily, most of which is excreted by the kidneys. The control of water and salt excretion in urine is very intricate, involving filtration by the glomerulus and reabsorption by the tubules of approximately 99% of the filtered load. The actual quantities excreted depend on the requirements prevailing at the moment. The finer adjustments of the tubular absorptive mechanisms are influenced by osmotic interrelationships between cell water, plasma and urine and by certain steroid hormones influencing electrolyte excretion and the posterior pituitary hormone regulating water excretion. When food intake ceases or salt is withheld, the content of sodium chloride in urine diminishes rapidly so that the body stores are retained. Similar renal retention of electrolyte occurs when salt is lost via gastrointestinal secretions through vomiting, etc. In other conditions, such as congestive heart failure, cirrhosis, nephritis or hypersecretion of the adrenal cortical hormones, the kidney fails to eliminate sufficient sodium. This results in retention of both salt and water, producing an excessive accumulation of extracellular fluid, which may be effectively combatted by a sharp restriction of salt intake and use of a diuretic.

Depletion of body salt may be caused in many ways, one of which is too energetic treatment of fluid and sodium retention. Besides this, diabetic acidosis, burns, excessive sweating with free drinking of water, repeated paracentesis for removal of ascitic fluid, adrenal cortical hypofunction and certain forms of nephritis, as well as abnormal losses of gastrointestinal secretions, will cause marked salt depletion. With salt loss, there is a reduction of the osmotic pressure of the extracellular fluid; the urine volume may be retained, but it is free of sodium chloride.

INDICATIONS AND USAGE

Sodium Chloride Injection, USP, 0.9% preparations are indicated for diluting or dissolving drugs for intravenous, intramuscular or subcutaneous injection according to instructions of the manufacturer of the drug to be administered.

Sodium Chloride Injection, USP, 0.9% is also indicated for use as an irrigation solution as well as for use in flushing of intravenous catheters.

WARNINGS

In flushing intravenous catheters with Sodium Chloride Injection, USP, 0.9%, only a preservative-free formulation should be used. Where a sodium chloride solution is required for preparing or diluting medications for use in newborns, only preservative-free Sodium Chloride Injection, USP, 0.9% should be used.

PRECAUTIONS

General

Sodium chloride must be used with caution in the presence of congestive heart failure, circulatory insufficiency, kidney dysfunction or hypoproteinemia.

Excessive amounts of sodium chloride by any route may cause hypopotassemia and acidosis. Excessive amounts by the parenteral route may precipitate congestive heart failure and acute pulmonary edema, especially in patients with cardiovascular disease and in patients receiving corticosteroids or corticotropin or drugs that may give rise to sodium retention.

Pregnancy Category C

Animal reproduction studies have not been conducted with Sodium Chloride Injection, USP, 0.9%. It is also not known whether Sodium Choride Injection can cause fetal harm when administered to a pregnant woman or can affect reproduction capacity. Sodium Chloride Injection, USP, 0.9% should be given to a pregnant woman only if clearly needed.

ADVERSE REACTIONS

Reactions which may occur because of this solution, added drugs or the technique of reconstitution or administration include febrile response, local tenderness, abscess, tissue necrosis or infection at the site of injection, venous thrombosis or phlebitis extending from the site of injection and extravasation.

If an adverse reaction does occur, discontinue the infusion, evaluate the patient, institute appropriate countermeasures, and if possible, retrieve and save the remainder of the unused vehicle for examination.

OVERDOSAGE

When used as a diluent, solvent, irrigation solution or intravascular flushing solution, this parenteral preparation is unlikely to pose a threat of sodium chloride or fluid overload except possibly in very small infants. In the event these should occur, reevaluate the patient and institute appropriate corrective measures. See PRECAUTIONS and ADVERSE REACTIONS.

DOSAGE AND ADMINISTRATION

Before Sodium Chloride Injection, USP, 0.9% is used as a vehicle for the administration of a drug, specific references should be checked for any possible incompatibility with sodium chloride.

The volume of the preparation to be used for diluting or dissolving any drug for injection is dependent on the vehicle concentration, dose and route of administration as recommended by the manufacturer.

Sodium Chloride Injection, USP, 0.9% is also indicated for use in flushing intravenous catheters. Prior to and after administration of the medication, the intravenous catheter must be flushed in its entirety with 2 mL of Sodium Chloride Injection, USP, 0.9%. Use in accord with any warnings or precautions appropriate to the medication being administered.

Parenteral drug products should be inspected visually for particulate matter and discoloration prior to administration, whenever solution and container permit.

HOW SUPPLIED

Sodium Chloride Injection, USP, 0.9%, is supplied as:

Product No | NDC No | Strength
186100 | 63323-186-00 | 0.9% | 100 mL single dose vial with a tear-off seal, in packages of 25.

Preservative free. Discard unused portion.

Use only if solution is clear and seal intact.

Store at 20° to 25°C (68° to 77°F) [see USP Controlled Room Temperature].

45786C

Revised: April 2008

PACKAGE LABEL

PACKAGE LABEL - PRINCIPAL DISPLAY - Sodium Chloride 100 mL Single Dose Vial Label

NDC 63323-186-00

186100

Sodium Chloride Injection, USP

0.9%

100 mL Single Dose Vial

Rx only